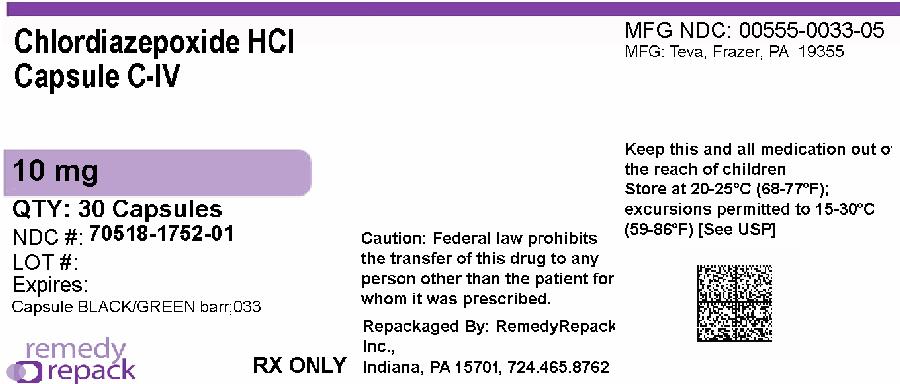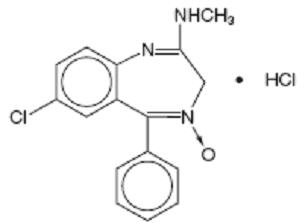 DRUG LABEL: Chlordiazepoxide Hydrochloride
NDC: 70518-1752 | Form: CAPSULE
Manufacturer: REMEDYREPACK INC.
Category: prescription | Type: HUMAN PRESCRIPTION DRUG LABEL
Date: 20260127
DEA Schedule: CIV

ACTIVE INGREDIENTS: CHLORDIAZEPOXIDE HYDROCHLORIDE 10 mg/1 1
INACTIVE INGREDIENTS: ANHYDROUS LACTOSE; D&C YELLOW NO. 10; FD&C BLUE NO. 1; FD&C RED NO. 40; GELATIN, UNSPECIFIED; HYDROGENATED COTTONSEED OIL; MICROCRYSTALLINE CELLULOSE; POVIDONE; PROPYLENE GLYCOL; SODIUM HYDROXIDE; SHELLAC; TITANIUM DIOXIDE

Chlordiazepoxide Hydrochloride Capsules, USP CIV
Rx only

WARNING: RISKS FROM CONCOMITANT USE WITH OPIOIDS; ABUSE, MISUSE, AND ADDICTION; and DEPENDENCE AND WITHDRAWAL REACTIONS

- Concomitant use of benzodiazepines and opioids may result in profound sedation, respiratory depression, coma, and death. Reserve concomitant prescribing of these drugs for patients for whom alternative treatment options are inadequate. Limit dosages and durations to the minimum required. Follow patients for signs and symptoms of respiratory depression and sedation (see WARNINGS and PRECAUTIONS).
- The use of benzodiazepines, including chlordiazepoxide hydrochloride capsules, exposes users to risks of abuse, misuse, and addiction, which can lead to overdose or death. Abuse and misuse of benzodiazepines commonly involve concomitant use of other medications, alcohol, and/or illicit substances, which is associated with an increased frequency of serious adverse outcomes. Before prescribing chlordiazepoxide hydrochloride capsules and throughout treatment, assess each patient’s risk for abuse, misuse, and addiction (see WARNINGS).
- The continued use of benzodiazepines, including chlordiazepoxide hydrochloride capsules, may lead to clinically significant physical dependence. The risks of dependence and withdrawal increase with longer treatment duration and higher daily dose. Abrupt discontinuation or rapid dosage reduction of chlordiazepoxide hydrochloride capsules after continued use may precipitate acute withdrawal reactions, which can be life-threatening. To reduce the risk of withdrawal reactions, use a gradual taper to discontinue chlordiazepoxide hydrochloride capsules or reduce the dosage (see DOSAGE AND ADMINISTRATION and WARNINGS).

DESCRIPTION

Chlordiazepoxide hydrochloride, USP is the prototype for the benzodiazepine compounds. It is a versatile therapeutic agent of proven value for the relief of anxiety. Chlordiazepoxide hydrochloride, USP is among the safer of the effective psychopharmacologic compounds available, as demonstrated by extensive clinical evidence.

Chlordiazepoxide hydrochloride, USP is 7-chloro-2-(methylamino)-5-phenyl-3 H-1,4-benzodiazepine 4-oxide hydrochloride. A white to practically white crystalline substance, it is soluble in water. It is unstable in solution and the powder must be protected from light. The structural formula is:

C16H14ClN3O • HCl M.W. 336.22

Each capsule, for oral administration, contains either 5 mg, 10 mg or 25 mg of chlordiazepoxide hydrochloride, USP and has the following inactive ingredients: anhydrous lactose, D&C yellow no. 10, FD&C blue no. 1, gelatin, hydrogenated vegetable oil, microcrystalline cellulose, pharmaceutical glaze, and titanium dioxide. The 5 mg and 25 mg also contain D&C yellow no. 10 aluminum lake, FD&C blue no. 1 aluminum lake, FD&C blue no. 2 aluminum lake, FD&C red no. 40 aluminum lake, and synthetic black iron oxide. In addition, the 5 mg contains D&C red no. 33 and the 10 mg also contains FD&C red no. 40, povidone, propylene glycol, and sodium hydroxide. The 5 mg and 25 mg may also contain propylene glycol.

CLINICAL PHARMACOLOGY

Chlordiazepoxide HCl has antianxiety, sedative, appetite-stimulating and weak analgesic actions. The precise mechanism of action is not known. The drug blocks EEG arousal from stimulation of the brain stem reticular formation. It takes several hours for peak blood levels to be reached and the half-life of the drug is between 24 and 48 hours. After the drug is discontinued plasma levels decline slowly over a period of several days. Chlordiazepoxide is excreted in the urine, with 1% to 2% unchanged and 3% to 6% as a conjugate.

Animal Pharmacology

The drug has been studied extensively in many species of animals and these studies are suggestive of action on the limbic system of the brain, which recent evidence indicates is involved in emotional responses.

Hostile monkeys were made tame by oral drug doses which did not cause sedation. Chlordiazepoxide HCl revealed a “taming” action with the elimination of fear and aggression. The taming effect of chlordiazepoxide HCl was further demonstrated in rats made vicious by lesions in the septal area of the brain. The drug dosage which effectively blocked the vicious reaction was well below the dose which caused sedation in these animals.

The LD50of parenterally administered chlordiazepoxide HCl was determined in mice (72 hours) and rats (5 days), and calculated according to the method of Miller and Tainter, with the following results: mice, IV, 123 ± 12 mg/kg; mice, IM, 366 ± 7 mg/kg; rats, IV, 120 ± 7 mg/kg; rats, IM, > 160 mg/kg.

Effects on Reproduction

Reproduction studies in rats fed 10, 20 and 80 mg/kg daily and bred through one or two matings showed no congenital anomalies, nor were there adverse effects on lactation of the dams or growth of the newborn. However, in another study at 100 mg/kg daily there was noted a significant decrease in the fertilization rate and a marked decrease in the viability and body weight of offspring which may be attributable to sedative activity, thus resulting in lack of interest in mating and lessened maternal nursing and care of the young. One neonate in each of the first and second matings in the rat reproduction study at the 100 mg/kg dose exhibited major skeletal defects. Further studies are in progress to determine the significance of these findings.

INDICATIONS AND USAGE

Chlordiazepoxide HCl capsules are indicated for the management of anxiety disorders or for the short term relief of symptoms of anxiety, withdrawal symptoms of acute alcoholism, and preoperative apprehension and anxiety. Anxiety or tension associated with the stress of everyday life usually does not require treatment with an anxiolytic.

The effectiveness of chlordiazepoxide HCl capsules in long term use, that is, more than 4 months, has not been assessed by systematic clinical studies. The physician should periodically reassess the usefulness of the drug for the individual patient.

CONTRAINDICATIONS

Chlordiazepoxide HCl capsules are contraindicated in patients with known hypersensitivity to the drug.

WARNINGS

Risks from Concomitant Use with Opioids

Concomitant use of benzodiazepines, including chlordiazepoxide, and opioids may result in profound sedation, respiratory depression, coma, and death. Because of these risks, reserve concomitant prescribing of these drugs for use in patients for whom alternative treatment options are inadequate.

Observational studies have demonstrated that concomitant use of opioid analgesics and benzodiazepines increases the risk of drug-related mortality compared to use of opioids alone. If a decision is made to prescribe chlordiazepoxide concomitantly with opioids, prescribe the lowest effective dosages and minimum durations of concomitant use, and follow patients closely for signs and symptoms of respiratory depression and sedation. In patients already receiving an opioid analgesic, prescribe a lower initial dose of chlordiazepoxide than indicated in the absence of an opioid and titrate based on clinical response. If an opioid is initiated in a patient already taking chlordiazepoxide, prescribe a lower initial dose of the opioid and titrate based upon clinical response.

Advise both patients and caregivers about the risks of respiratory depression and sedation when chlordiazepoxide is used with opioids. Advise patients not to drive or operate heavy machinery until the effects of concomitant use with the opioid have been determined (see DRUG INTERACTIONS).

Abuse, Misuse, and Addiction

The use of benzodiazepines, including chlordiazepoxide, exposes users to the risks of abuse, misuse, and addiction, which can lead to overdose or death. Abuse and misuse of benzodiazepines often (but not always) involve the use of doses greater than the maximum recommended dosage and commonly involve concomitant use of other medications, alcohol, and/or illicit substances, which is associated with an increased frequency of serious adverse outcomes, including respiratory depression, overdose, or death (see DRUG ABUSE AND DEPENDENCE: Abuse) .

Before prescribing chlordiazepoxide and throughout treatment, assess each patient’s risk for abuse, misuse, and addiction (e.g., using a standardized screening tool). Use of chlordiazepoxide, particularly in patients at elevated risk, necessitates counseling about the risks and proper use of chlordiazepoxide along with monitoring for signs and symptoms of abuse, misuse, and addiction. Prescribe the lowest effective dosage; avoid or minimize concomitant use of CNS depressants and other substances associated with abuse, misuse, and addiction (e.g., opioid analgesics, stimulants); and advise patients on the proper disposal of unused drug. If a substance use disorder is suspected, evaluate the patient and institute (or refer them for) early treatment, as appropriate.

Dependence and Withdrawal Reactions

To reduce the risk of withdrawal reactions, use a gradual taper to discontinue chlordiazepoxide or reduce the dosage (a patient-specific plan should be used to taper the dose) (see DOSAGE AND ADMINISTRATION: Discontinuation or Dosage Reduction of chlordiazepoxide).

Patients at an increased risk of withdrawal adverse reactions after benzodiazepine discontinuation or rapid dosage reduction include those who take higher dosages, and those who have had longer durations of use.

Acute Withdrawal Reactions

The continued use of benzodiazepines, including chlordiazepoxide, may lead to clinically significant physical dependence. Abrupt discontinuation or rapid dosage reduction of chlordiazepoxide after continued use, or administration of flumazenil (a benzodiazepine antagonist) may precipitate acute withdrawal reactions, which can be life-threatening (e.g., seizures) (see DRUG ABUSE AND DEPENDENCE: Dependence) .

Protracted Withdrawal Syndrome

In some cases, benzodiazepine users have developed a protracted withdrawal syndrome with withdrawal symptoms lasting weeks to more than 12 months (see DRUG ABUSE AND DEPENDENCE: Dependence).

Chlordiazepoxide HCl may impair the mental and/or physical abilities required for the performance of potentially hazardous tasks such as driving a vehicle or operating machinery. Similarly, it may impair mental alertness in children. The concomitant use of alcohol or other central nervous system depressants may have an additive effect. PATIENTS SHOULD BE WARNED ACCORDINGLY.

Neonatal Sedation and Withdrawal Syndrome

Use of chlordiazepoxide HCl late in pregnancy can result in sedation (respiratory depression, lethargy, hypotonia) and/or withdrawal symptoms (hyperreflexia, irritability, restlessness, tremors, inconsolable crying, and feeding difficulties) in the neonate (see PRECAUTIONS, Pregnancy) .Monitor neonates exposed to chlordiazepoxide HCl during pregnancy or labor for signs of sedation and monitor neonates exposed to chlordiazepoxide HCl during pregnancy for signs of withdrawal; manage these neonates accordingly.

PRECAUTIONS

In elderly and debilitated patients, it is recommended that the dosage be limited to the smallest effective amount to preclude the development of ataxia or oversedation (10 mg or less per day initially, to be increased gradually as needed and tolerated). In general, the concomitant administration of chlordiazepoxide HCl and other psychotropic agents is not recommended. If such combination therapy seems indicated, careful consideration should be given to the pharmacology of the agents to be employed particularly when the known potentiating compounds such as MAO inhibitors and phenothiazines are to be used. The usual precautions in treating patients with impaired renal or hepatic function should be observed.

Paradoxical reactions, e.g., excitement, stimulation and acute rage, have been reported in psychiatric patients and in hyperactive aggressive pediatric patients, and should be watched for during chlordiazepoxide HCl therapy. The usual precautions are indicated when chlordiazepoxide HCl is used in the treatment of anxiety states where there is any evidence of impending depression; it should be borne in mind that suicidal tendencies may be present and protective measures may be necessary. Although clinical studies have not established a cause and effect relationship, physicians should be aware that variable effects on blood coagulation have been reported very rarely in patients receiving oral anticoagulants and chlordiazepoxide HCl. In view of isolated reports associating chlordiazepoxide with exacerbation of porphyria, caution should be exercised in prescribing chlordiazepoxide to patients suffering from this disease.

Pediatric Use

Because of the varied response of pediatric patients to CNS-acting drugs, therapy should be initiated with the lowest dose and increased as required (see DOSAGE AND ADMINISTRATION). Since clinical experience with chlordiazepoxide HCl in pediatric patients under 6 years of age is limited, use in this age group is not recommended. Hyperactive aggressive pediatric patients should be monitored for paradoxical reactions to chlordiazepoxide HCl (see PRECAUTIONS).

Information for Patients

Advise the patient to read the FDA-approved patient labeling (Medication Guide).

Repackaged By / Distributed By: RemedyRepack Inc.

625 Kolter Drive, Indiana, PA 15701

(724) 465-8762

Risks from Concomitant Use with Opioids

Advise both patients and caregivers about the risks of potentially fatal respiratory depression and sedation when chlordiazepoxide is used with opioids and not to use such drugs concomitantly unless supervised by a health care provider. Advise patients not to drive or operate heavy machinery until the effects of concomitant use with the opioid have been determined (see WARNINGS: Risks from Concomitant Use with Opioids and PRECAUTIONS: Drug Interactions).

Abuse, Misuse, and Addiction

Inform patients that the use of chlordiazepoxide, even at recommended dosages, exposes users to risks of abuse, misuse, and addiction, which can lead to overdose and death, especially when used in combination with other medications (e.g., opioid analgesics), alcohol, and/or illicit substances. Inform patients about the signs and symptoms of benzodiazepine abuse, misuse, and addiction; to seek medical help if they develop these signs and/or symptoms; and on the proper disposal of unused drug (see WARNINGS: Abuse, Misuse, and Addiction and DRUG ABUSE AND DEPENDENCE).

Withdrawal Reactions

Inform patients that the continued use of chlordiazepoxide may lead to clinically significant physical dependence and that abrupt discontinuation or rapid dosage reduction of chlordiazepoxide may precipitate acute withdrawal reactions, which can be life-threatening. Inform patients that in some cases, patients taking benzodiazepines have developed a protracted withdrawal syndrome with withdrawal symptoms lasting weeks to more than 12 months. Instruct patients that discontinuation or dosage reduction of chlordiazepoxide may require a slow taper (see WARNINGS: Dependence and Withdrawal Reactions and DRUG ABUSE AND DEPENDENCE).

Pregnancy

Advise pregnant females that use of chlordiazepoxide HCl late in pregnancy can result in sedation (respiratory depression, lethargy, hypotonia) and/or withdrawal symptoms (hyperreflexia, irritability, restlessness, tremors, inconsolable crying, and feeding difficulties) in newborns (see Warnings, Neonatal Sedation and Withdrawal Syndromeand Precautions, Pregnancy). Instruct patients to inform their healthcare provider if they are pregnant.

Advise patients that there is a pregnancy exposure registry that monitors pregnancy outcomes in women exposed to chlordiazepoxide HCl during pregnancy (see Precautions, Pregnancy) .

Nursing

Advise patients that breastfeeding is not recommended during treatment with chlordiazepoxide HCl (see Precautions, Nursing Mothers).

Drug Interactions

The concomitant use of benzodiazepines and opioids increases the risk of respiratory depression because of actions at different receptor sites in the CNS that control respiration. Benzodiazepines interact at GABAAsites and opioids interact primarily at mu receptors. When benzodiazepines and opioids are combined, the potential for benzodiazepines to significantly worsen opioid-related respiratory depression exists. Limit dosage and duration of concomitant use of benzodiazepines and opioids, and monitor patients closely for respiratory depression and sedation.

Pregnancy:

Pregnancy Exposure Registry

There is a pregnancy registry that monitors pregnancy outcomes in women exposed to psychiatric medications, including chlordiazepoxide HCl, during pregnancy. Healthcare providers are encouraged to register patients by calling the National Pregnancy Registry for Psychiatric Medications at
1-866-961-2388 or visiting online at https://womensmentalhealth.org/pregnancyregistry/.

Risk Summary

Neonates born to mothers using benzodiazepines late in pregnancy have been reported to experience symptoms of sedation and/or neonatal withdrawal (see WARNINGS, Neonatal Sedation and Withdrawal Syndrome, and Clinical Considerations) .Available data from published observational studies of pregnant women exposed to benzodiazepines do not report a clear association with benzodiazepines and major birth defects (see Data).

The background risk of major birth defects and miscarriage for the indicated population is unknown. All pregnancies have a background risk of birth defect, loss, or other adverse outcomes. In the U.S. general population, the estimated risk of major birth defects and of miscarriage in clinically recognized pregnancies is 2% to 4% and 15% to 20%, respectively.

Clinical Considerations

Fetal/Neonatal Adverse Reactions

Benzodiazepines cross the placenta and may produce respiratory depression, hypotonia and sedation in neonates. Monitor neonates exposed to chlordiazepoxide HCl during pregnancy or labor for signs of sedation, respiratory depression, hypotonia, and feeding problems. Monitor neonates exposed to chlordiazepoxide HCl during pregnancy for signs of withdrawal. Manage these neonates accordingly (see WARNINGS, Neonatal Sedation and Withdrawal Syndrome) .

Data

Human Data

Published data from observational studies on the use of benzodiazepines during pregnancy do not report a clear association with benzodiazepines and major birth defects. Although early studies reported an increased risk of congenital malformations with diazepam and chlordiazepoxide, there was no consistent pattern noted. In addition, the majority of more recent case-control and cohort studies of benzodiazepine use during pregnancy, which were adjusted for confounding exposures to alcohol, tobacco and other medications, have not confirmed these findings.

Nursing:

Risk Summary

There are no data on the presence of chlordiazepoxide in human milk. There are reports of sedation, poor feeding and poor weight gain in infants exposed to benzodiazepines through breast milk. Because of chlordiazepoxide’s long half-life, the potential for chlordiazepoxide to accumulate in breast milk and the potential for serious adverse reactions, including sedation and withdrawal symptoms in breastfed infants, advise patients that breastfeeding is not recommended during treatment with chlordiazepoxide HCl.

ADVERSE REACTIONS

The necessity of discontinuing therapy because of undesirable effects has been rare. Drowsiness, ataxia and confusion have been reported in some patients particularly the elderly and debilitated. While these effects can be avoided in almost all instances by proper dosage adjustment, they have occasionally been observed at the lower dosage ranges. In a few instances syncope has been reported.

Other adverse reactions reported during therapy include isolated instances of skin eruptions, edema, minor menstrual irregularities, nausea and constipation, extrapyramidal symptoms, as well as increased and decreased libido. Such side effects have been infrequent, and are generally controlled with reduction of dosage. Changes in EEG patterns (low-voltage fast activity) have been observed in patients during and after chlordiazepoxide HCl treatment.

Blood dyscrasias (including agranulocytosis), jaundice and hepatic dysfunction have occasionally been reported during therapy. When chlordiazepoxide HCl treatment is protracted, periodic blood counts and liver function tests are advisable.

To report SUSPECTED ADVERSE EVENTS, contact Teva at 1-888-838-2872 or FDA at 1-800-FDA-1088 or http://www.fda.gov/medwatch for voluntary reporting of adverse reactions.

DRUG ABUSE AND DEPENDENCE

Controlled Substance

Chlordiazepoxide is a Schedule IV controlled substance.

Abuse

Chlordiazepoxide is a benzodiazepine and a CNS depressant with a potential for abuse and addiction. Abuse is the intentional, non-therapeutic use of a drug, even once, for its desirable psychological or physiological effects. Misuse is the intentional use, for therapeutic purposes, of a drug by an individual in a way other than prescribed by a health care provider or for whom it was not prescribed. Drug addiction is a cluster of behavioral, cognitive, and physiological phenomena that may include a strong desire to take the drug, difficulties in controlling drug use (e.g., continuing drug use despite harmful consequences, giving a higher priority to drug use than other activities and obligations), and possible tolerance or physical dependence. Even taking benzodiazepines as prescribed may put patients at risk for abuse and misuse of their medication. Abuse and misuse may lead to addiction.

Abuse and misuse of benzodiazepines often (but not always) involve the use of doses greater than the maximum recommended dosage and commonly involve concomitant use of other medications, alcohol, and/or illicit substances, which is associated with an increased frequency of serious adverse outcomes, including respiratory depression, overdose, or death. Benzodiazepines are often sought by individuals who abuse drugs and other substances, and by individuals with addictive disorders (see WARNINGS: Abuse, Misuse, and Addiction).

The following adverse reactions have occurred with benzodiazepine abuse and/or misuse: abdominal pain, amnesia, anorexia, anxiety, aggression, ataxia, blurred vision, confusion, depression, disinhibition, disorientation, dizziness, euphoria, impaired concentration and memory, indigestion, irritability, muscle pain, slurred speech, tremors, and vertigo.

The following severe adverse reactions have occurred with benzodiazepine abuse and/or misuse: delirium, paranoia, suicidal ideation and behavior, seizures, coma, breathing difficulty, and death. Death is more often associated with polysubstance use (especially benzodiazepines with other CNS depressants such as opioids and alcohol).

Dependence

Physical Dependence

Chlordiazepoxide may produce physical dependence from continued therapy. Physical dependence is a state that develops as a result of physiological adaptation in response to repeated drug use, manifested by withdrawal signs and symptoms after abrupt discontinuation or a significant dose reduction of a drug. Abrupt discontinuation or rapid dosage reduction of benzodiazepines or administration of flumazenil, a benzodiazepine antagonist, may precipitate acute withdrawal reactions, including seizures, which can be life-threatening. Patients at an increased risk of withdrawal adverse reactions after benzodiazepine discontinuation or rapid dosage reduction include those who take higher dosages (i.e., higher and/or more frequent doses) and those who have had longer durations of use (see WARNINGS: Dependence and Withdrawal Reactions).

To reduce the risk of withdrawal reactions, use a gradual taper to discontinue chlordiazepoxide or reduce the dosage (see DOSAGE AND ADMINISTRATION: Discontinuation or Dosage Reduction of Chlordiazepoxide and WARNINGS: Dependence and Withdrawal Reactions).

Acute Withdrawal Signs and Symptoms

Acute withdrawal signs and symptoms associated with benzodiazepines have included abnormal involuntary movements, anxiety, blurred vision, depersonalization, depression, derealization, dizziness, fatigue, gastrointestinal adverse reactions (e.g., nausea, vomiting, diarrhea, weight loss, decreased appetite), headache, hyperacusis, hypertension, irritability, insomnia, memory impairment, muscle pain and stiffness, panic attacks, photophobia, restlessness, tachycardia, and tremor. More severe acute withdrawal signs and symptoms, including life-threatening reactions, have included catatonia, convulsions, delirium tremens, depression, hallucinations, mania, psychosis, seizures, and suicidality.

Protracted Withdrawal Syndrome

Protracted withdrawal syndrome associated with benzodiazepines is characterized by anxiety, cognitive impairment, depression, insomnia, formication, motor symptoms (e.g., weakness, tremor, muscle twitches), paresthesia, and tinnitus that persists beyond 4 to 6 weeks after initial benzodiazepine withdrawal. Protracted withdrawal symptoms may last weeks to more than 12 months. As a result, there may be difficulty in differentiating withdrawal symptoms from potential re-emergence or continuation of symptoms for which the benzodiazepine was being used.

Tolerance

Tolerance to Chlordiazepoxide may develop from continued therapy. Tolerance is a physiological state characterized by a reduced response to a drug after repeated administration (i.e., a higher dose of a drug is required to produce the same effect that was once obtained at a lower dose). Tolerance to the therapeutic effect of chlordiazepoxide may develop; however, little tolerance develops to the amnestic reactions and other cognitive impairments caused by benzodiazepines.

Overdosage

Overdosage of benzodiazepines is characterized by central nervous system depression ranging from drowsiness to coma. In mild to moderate cases, symptoms can include drowsiness, confusion, dysarthria, lethargy, hypnotic state, diminished reflexes, ataxia, and hypotonia. Rarely, paradoxical or disinhibitory reactions (including agitation, irritability, impulsivity, violent behavior, confusion, restlessness, excitement, and talkativeness) may occur. In severe overdosage cases, patients may develop respiratory depression and coma. Overdosage of benzodiazepines in combination with other CNS depressants (including alcohol and opioids) may be fatal (see WARNINGS: Abuse, Misuse, and Addiction). Markedly abnormal (lowered or elevated) blood pressure, heart rate, or respiratory rate raise the concern that additional drugs and/or alcohol are involved in the overdosage.

In managing benzodiazepine overdosage, employ general supportive measures, including intravenous fluids and airway management. Flumazenil, a specific benzodiazepine receptor antagonist indicated for the complete or partial reversal of the sedative effects of benzodiazepines in the management of benzodiazepine overdosage, can lead to withdrawal and adverse reactions, including seizures, particularly in the context of mixed overdosage with drugs that increase seizure risk (e.g., tricyclic and tetracyclic antidepressants) and in patients with long-term benzodiazepine use and physical dependency. The risk of withdrawal seizures with flumazenil use may be increased in patients with epilepsy. Flumazenil is contraindicated in patients who have received a benzodiazepine for control of a potentially life-threatening condition (e.g., status epilepticus). If the decision is made to use flumazenil, it should be used as an adjunct to, not as a substitute for, supportive management of benzodiazepine overdosage. See the flumazenil injection Prescribing Information.

Consider contacting a poison center (1-800-222-1222), poisoncontrol.org, or medical toxicologist for additional overdosage management recommendations.

DOSAGE AND ADMINISTRATION

Because of the wide range of clinical indications for chlordiazepoxide HCl, the optimum dosage varies with the diagnosis and response of the individual patient. The dosage, therefore, should be individualized for maximum beneficial effects.

ADULTS | USUAL DAILY DOSE
Relief of Mild and Moderate Anxiety Disorders and Symptoms of Anxiety | 5 mg or 10 mg, 3 or 4 times daily
Relief of Severe Anxiety Disorders and Symptoms of Anxiety | 20 mg or 25 mg, 3 or 4 times daily
Geriatric Patients, or in the presence of debilitating disease. | 5 mg, 2 to 4 times daily

Preoperative Apprehension and Anxiety

On days preceding surgery, 5 to 10 mg orally, 3 or 4 times daily. If used as preoperative medication, 50 to 100 mg IM 1 hour prior to surgery.

PEDIATRIC PATIENTS | USUAL DAILY DOSE
Because of the varied response of pediatric patients to CNS-acting drugs, therapy should be initiated with the lowest dose and increased as required. Since clinical experience in pediatric patients under 6 years of age is limited, the use of the drug in this age group is not recommended. | 5 mg, 2 to 4 times daily (may be increased in some pediatric patients to 10 mg, 2 to 3 times daily)

For the relief of withdrawal symptoms of acute alcoholism, the parenteral form is usually used initially. If the drug is administered orally, the suggested initial dose is 50 to 100 mg, to be followed by repeated doses as needed until agitation is controlled up to 300 mg per day. Dosage should then be reduced to maintenance levels.

*See package insert for Sterile Chlordiazepoxide Hydrochloride.

Discontinuation or Dosage Reduction of Chlordiazepoxide

To reduce the risk of withdrawal reactions, use a gradual taper to discontinue chlordiazepoxide or reduce the dosage. If a patient develops withdrawal reactions, consider pausing the taper or increase the dosage to the previous tapered dosage level. Subsequently decrease the dosage more slowly (see WARNINGS: Dependence and Withdrawal Reactions and DRUG ABUSE AND DEPENDENCE: Dependence).

HOW SUPPLIED

Chlordiazepoxide Hydrochloride Capsules USP, 10 mg are available as a two-piece hard gelatin capsule with a black opaque cap and a green opaque body filled with white powder, imprinted in white ink “stylized barr” 033, packaged in

NDC: 70518-1752-00

NDC: 70518-1752-01

PACKAGING: 30 in 1 BLISTER PACK

PACKAGING: 30 in 1 BLISTER PACK

Dispense in a tight, light-resistant container as defined in the USP, with a child-resistant closure (as required).

Store at 20° to 25°C (68° to 77°F) [See USP Controlled Room Temperature] in a dry place.

Keep this and all medications out of the reach of children.

Repackaged and Distributed By:

Remedy Repack, Inc.

625 Kolter Dr. Suite #4 Indiana, PA 1-724-465-8762

MEDICATION GUIDE

Chlordiazepoxide Hydrochloride (klorʺ dye azʺ e poxʹ ide hyeʺ droe klorʹ ide) Capsules, C-IV

What is the most important information I should know about Chlordiazepoxide HCl?

- Chlordiazepoxide HCl is a benzodiazepine medicine. Taking benzodiazepines with opioid medicines, alcohol, or other central nervous system depressants (CNS) (including street drugs) can cause severe drowsiness, breathing problems (respiratory depression), coma and death. Get emergency help right away if any of the following happens:

- shallow or slowed breathing
- breathing stops (which may lead to the heart stopping)
- excessive sleepiness (sedation)

Do not drive or operate heavy machinery until you know how taking Chlordiazepoxide HCl with opioids affects you.

- Risk of abuse, misuse, and addiction.There is a risk of abuse, misuse, and addiction with benzodiazepines, including Chlordiazepoxide HCl, which can lead to overdose and serious side effects including coma and death.
  - Serious side effects including coma and death have happened in people who have abused or misused benzodiazepines, including Chlordiazepoxide HCl.These serious side effects may also include delirium, paranoia, suicidal thoughts or actions, seizures, and difficulty breathing. Call your healthcare provider or go to the nearest hospital emergency room right away if you get any of these serious side effects.
  - You can develop an addiction even if you take Chlordiazepoxide HCl exactly as prescribed by your healthcare provider.
  - Take Chlordiazepoxide HCl exactly as your healthcare provider prescribed.
  - Do not share your Chlordiazepoxide HCl with other people.
  - Keep Chlordiazepoxide HCl in a safe place and away from children.
- Physical dependence and withdrawal reactions. Chlordiazepoxide HCl can cause physical dependence and withdrawal reactions, especially if you continue to take Chlordiazepoxide HCl for several days to several weeks.

- Do not suddenly stop taking Chlordiazepoxide HCl. Stopping Chlordiazepoxide HCl suddenly can cause serious and life-threatening side effects, including unusual movements, responses, or expressions, seizures, sudden and severe mental or nervous system changes, depression, seeing or hearing things that others do not see or hear, an extreme increase in activity or talking, losing touch with reality, and suicidal thoughts or actions. Call your healthcare provider or go to the nearest hospital emergency room right awayif you get any of these symptoms.
- Some people who suddenly stop benzodiazepines have symptoms that can last for several weeks tomore than 12 months , including, anxiety, trouble remembering, learning, or concentrating, depression, problems sleeping feeling like insects are crawling under your skin, weakness, shaking, muscle twitching, burning or prickling feeling in your hands, arms, legs or feet, and ringing in your ears.
- Physical dependence is not the same as drug addiction. Your healthcare provider can tell you more about the differences between physical dependence and drug addiction.
- Do not take more Chlordiazepoxide HCl than prescribed or take Chlordiazepoxide HCl for longer than prescribed.

What is Chlordiazepoxide HCl?

- Chlordiazepoxide HCl is a prescription medicine used:
  - to treat anxiety disorders
  - for the short-term relief of the symptoms of anxiety
  - to treat withdrawal symptoms of acute alcoholism
  - preoperatively to treat apprehension and anxiety
- Chlordiazepoxide HCl is a federal controlled substance (C-IV) because it contains chlordiazepoxide that can be abused or lead to dependence.Keep Chlordiazepoxide HCl in a safe place to prevent misuse and abuse. Selling or giving away Chlordiazepoxide HCl may harm others, and is against the law. Tell your healthcare provider if you have abused or been dependent on alcohol, prescription medicines or street drugs.
- It is not known if Chlordiazepoxide HCl is safe and effective in children under 6 years of age.
- It is not known if Chlordiazepoxide HCl is safe and effective for use for longer than 4 months.

Do not takeChlordiazepoxide HCl if you are allergic to chlordiazepoxide or to any of the ingredients in Chlordiazepoxide HCl capsules. See the end of this Medication Guide for a complete list of ingredients in Chlordiazepoxide HCl capsules.

Before you take Chlordiazepoxide HCl, tell your healthcare provider about all of your medical conditions, including if you:

- have or have had depression, mood problems, or suicidal thoughts or behavior
- have a history of drug or alcohol abuse or addiction
- have liver or kidney problems
- are pregnant or plan to become pregnant.
  - Taking Chlordiazepoxide HCl late in pregnancy may cause your baby to have symptoms of sedation (breathing problems, sluggishness, low muscle tone), and/or withdrawal symptoms (jitteriness, irritability, restlessness, shaking, excessive crying, feeding problems).
  - Tell your healthcare provider right away if you become pregnant or think you are pregnant during treatment with Chlordiazepoxide HCl.
  - There is a pregnancy registry for women who take Chlordiazepoxide HCl during pregnancy. The purpose of the registry is to collect information about the health of you and your baby. If you become pregnant during treatment with Chlordiazepoxide HCl, talk to your healthcare provider about registering with the National Pregnancy Registry for Psychiatric Medications. You can register by calling 1-866-961-2388 or visiting https://womansmentalhealth.org/pregnancyregistry/.
- are breastfeeding or plan to breastfeed. Chlordiazepoxide HCl may pass into your breast milk.
  - Talk to your healthcare provider about the best way to feed your baby if you take Chlordiazepoxide HCl.
  - Breastfeeding is not recommended during treatment with Chlordiazepoxide HCl.

Tell your healthcare provider about all the medicines you take,including prescription and over-the-counter medicines, vitamins, and herbal supplements.

Taking Chlordiazepoxide HCl with certain other medicines can cause side effects or affect how well Chlordiazepoxide HCl or the other medicines work.

Ask your healthcare provider if you are not sure if you are taking any of these medicines. Your healthcare provider can tell you if it is safe to take Chlordiazepoxide HCl with your other medicines.

Do not start or stop any other medicines during treatment with Chlordiazepoxide HCl without talking to your healthcare provider first. Stopping Chlordiazepoxide HCl suddenly may cause you to have serious side effects. See, “What are the possible side effects of Chlordiazepoxide HCl?”

Know the medicines you take. Keep a list of them to show to your healthcare provider and pharmacist when you get a new medicine.

How should I take Chlordiazepoxide HCl?

- Take Chlordiazepoxide HCl exactly as your healthcare provider tells you to take it.
- If you take too much Chlordiazepoxide HCl, call your healthcare provider or go to the nearest hospital emergency room right away.

What are the possible side effects of Chlordiazepoxide HCl?

Chlordiazepoxide HCl may cause serious side effects, including:

- See “What is the most important information I should know about Chlordiazepoxide HCl?”
- Chlordiazepoxide HCl can make you sleepy or dizzy and can slow your thinking and motor skills.

- Do not drive, operate heavy machinery, or do other dangerous activities until you know how Chlordiazepoxide HCl affects you.
- Do not drink alcohol or take other drugs that may make you sleepy or dizzy while taking Chlordiazepoxide HCl without first talking to your healthcare provider. When taken with alcohol or drugs that cause sleepiness or dizziness, Chlordiazepoxide HCl may make your sleepiness or dizziness much worse.

The most common side effects of Chlordiazepoxide HCl include:

- drowsiness

- loss of control of body movements (ataxia)

- confusion

These are not all the possible side effects of chlordiazepoxide. Call your doctor for medical advice about side effects. You may report side effects to FDA at 1-800-FDA-1088.

How should I store Chlordiazepoxide HCl?

- Store Chlordiazepoxide HCl at room temperature between 68°F to 77°F (20°C to 25°C).
- Keep Chlordiazepoxide HCl capsules in a tightly closed container and out of the light.
- Keep Chlordiazepoxide HCl and all medicines out of the reach of children.

General information about the safe and effective use of Chlordiazepoxide HCl.

Medicines are sometimes prescribed for purposes other than those listed in a Medication Guide. Do not use Chlordiazepoxide HCl for a condition for which it was not prescribed. Do not give Chlordiazepoxide HCl to other people, even if they have the same symptoms that you have. It may harm them. You can ask your pharmacist or healthcare provider for information about Chlordiazepoxide HCl that is written for health professionals.

What are the ingredients in Chlordiazepoxide HCl?

Active ingredient:chlordiazepoxide hydrochloride

Inactive ingredients:anhydrous lactose, D&C yellow no. 10, FD&C blue no. 1, gelatin, hydrogenated vegetable oil, microcrystalline cellulose, pharmaceutical glaze, and titanium dioxide. The 5 mg and 25 mg also contain D&C yellow no. 10 aluminum lake, FD&C blue no. 1 aluminum lake, FD&C blue no. 2 aluminum lake, FD&C red no. 40 aluminum lake, and synthetic black iron oxide. In addition, the 5 mg contains D&C red no. 33 and the 10 mg also contains FD&C red no. 40, povidone, propylene glycol, and sodium hydroxide. The 5 mg and 25 mg may also contain propylene glycol.

This Medication Guide has been approved by the U.S. Food and Drug Administration Rev. H 6/2025

Repackaged By / Distributed By: RemedyRepack Inc.

625 Kolter Drive, Indiana, PA 15701

(724) 465-8762

PACKAGE LABEL

DRUG: Chlordiazepoxide Hydrochloride

GENERIC: Chlordiazepoxide Hydrochloride

DOSAGE: CAPSULE

ADMINSTRATION: ORAL

NDC: 70518-1752-0

NDC: 70518-1752-1

COLOR: black

SHAPE: CAPSULE

SCORE: No score

SIZE: 14 mm

IMPRINT: barr;033

PACKAGING: 30 in 1 BLISTER PACK

PACKAGING: 30 in 1 BLISTER PACK

ACTIVE INGREDIENT(S):

- CHLORDIAZEPOXIDE HYDROCHLORIDE 10mg in 1

INACTIVE INGREDIENT(S):

- ANHYDROUS LACTOSE
- D&C YELLOW NO. 10
- FD&C BLUE NO. 1
- FD&C RED NO. 40
- GELATIN, UNSPECIFIED
- HYDROGENATED COTTONSEED OIL
- MICROCRYSTALLINE CELLULOSE
- POVIDONE
- PROPYLENE GLYCOL
- SODIUM HYDROXIDE
- SHELLAC
- TITANIUM DIOXIDE